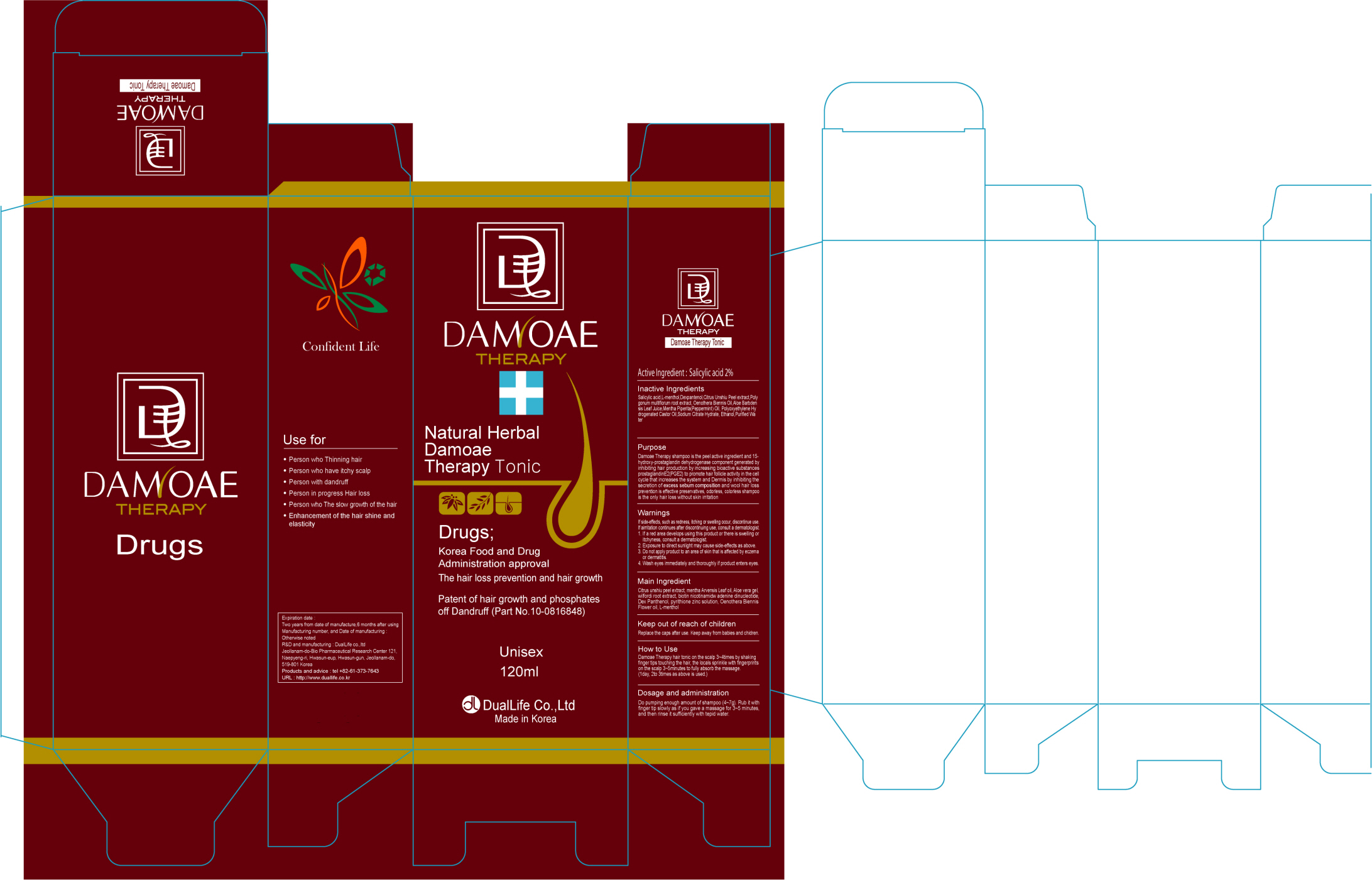 DRUG LABEL: DAMOAE THERAPY TONIC
NDC: 76081-020 | Form: SOLUTION
Manufacturer: DUALLIFE CO., LTD.
Category: otc | Type: HUMAN OTC DRUG LABEL
Date: 20120206

ACTIVE INGREDIENTS: SALICYLIC ACID 2.4 mL/120 mL
INACTIVE INGREDIENTS: LEVOMENTHOL; FALLOPIA MULTIFLORA ROOT; OENOTHERA BIENNIS; ALOE VERA LEAF; PEPPERMINT OIL; ALCOHOL; WATER

Drug Facts

Active Ingredient: Salicylic acid 2%

Inactive Ingredients:
L-menthol, Dexpantenol, Citrus Unshiu Peel extract, polygonum multiflorum root extract, Oenothera Biennis Oil, Aloe Barbadensis Leaf Juice, Mentha Piperita (Peppermint) Oil, Polyoxyethylene Hydrogenated Castor Oil, Sodium Citrate Hydrate, Ethanol, Purified Water

Purpose: Dandruff

WARNINGS:
If side-effects, such as redness, itching or swelling occur, discontinue use. If airritation continues after discontinuing use, consult a dermatologist.
1. If a red area develops using this product or there is swelling or itchyness, consult a dermatologist.
2. Exposure to direct sunlight may cause side-effects as above.
3. Do not apply product to an area of skin that is affected by eczema or dermatitis.
4. Wash eyes immediately and thoroughly if product enters eyes.

Keep out of reach of children:
Replace the caps after use.
Keep away from babies and children.

Indication and usage:
Damoae Therapy hair tonic on the scalp 3-4 times by shaking finger tips touching the hair, the locals sprinkle with fingerprints on the scalp 3-5 minutes to fully absorb the massage.
- 1 day , 2 to 3 times as above is used.

Dosage and administration:
Do pumping enough amount of hair tonic (2-3 times). Rub it with finger tip slowly as if you gave a massage for 3-5 minutes.